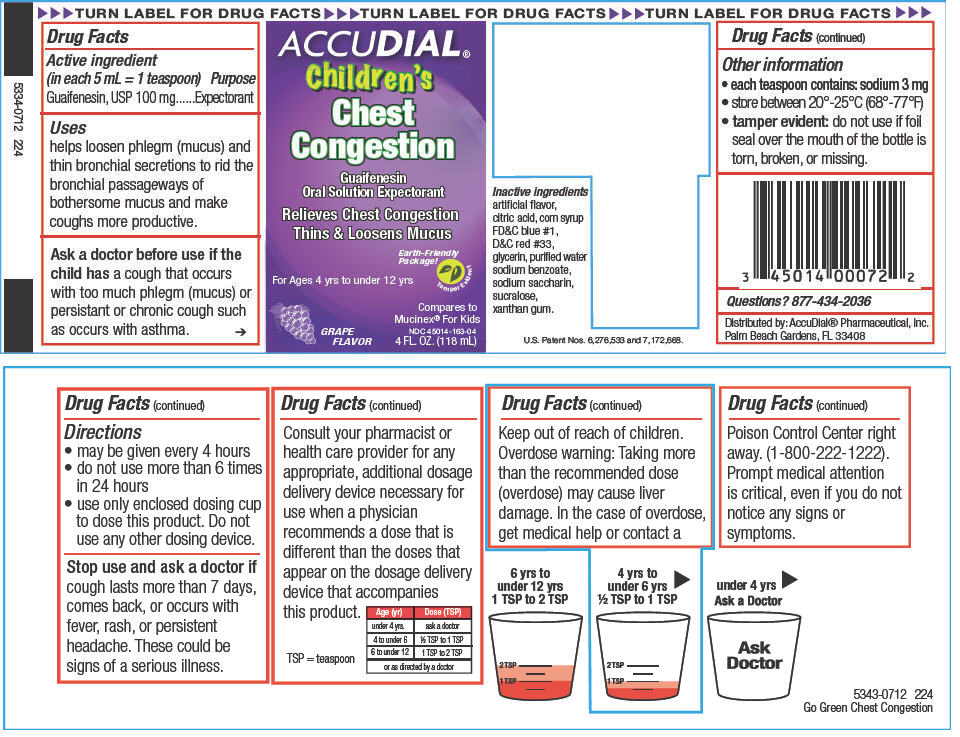 DRUG LABEL: Chest Congestion
NDC: 45014-163 | Form: SOLUTION
Manufacturer: Accudial Pharmaceutical, Inc.
Category: otc | Type: HUMAN OTC DRUG LABEL
Date: 20130206

ACTIVE INGREDIENTS: Guaifenesin 100 mg/5 mL
INACTIVE INGREDIENTS: Citric Acid Monohydrate; Corn Syrup; FD&C Blue No. 1; D&C Red No. 33; Glycerin; Water; Sodium Benzoate; Saccharin Sodium; Sucralose; Xanthan Gum

Chest Congestion

Drug Facts

Active ingredient (in each 5 mL = 1 teaspoon)

Guaifenesin, USP 100 mg

Purpose

Expectorant

Uses

helps loosen phlegm (mucus) and thin bronchial secretions to rid the bronchial passageways of bothersome mucus and make coughs more productive.

WARNINGS

Ask a doctor before use if the child has a cough that occurs with too much phlegm (mucus) or persistant or chronic cough such as occurs with asthma.

Directions

- may be given every 4 hours
- do not use more than 6 times in 24 hours
- use only enclosed dosing cup to dose this product. Do not use any other dosing device.

Stop use and ask a doctor if cough lasts more than 7 days, comes back, or occurs with fever, rash, or persistent headache. These could be signs of a serious illness.

ASK DOCTOR/PHARMACIST

Consult your pharmacist or health care provider for any appropriate, additional dosage delivery device necessary for use when a physician recommends a dose that is different than the doses that appear on the dosage delivery device that accompanies this product.

Age (yr) | Dose (TSP)
under 4 yrs. | ask a doctor
4 to under 6 | ½ TSP to 1 TSP
6 to under 12 | 1 TSP to 2 TSP
or as directed by a doctor
TSP = teaspoon

Keep out of reach of children.

Overdose warning

Taking more than the recommended dose (overdose) may cause liver damage. In the case of overdose, get medical help or contact a Poison Control Center right away. (1-800-222-1222). Prompt medical attention is critical, even if you do not notice any signs or symptoms.

Other information

- each teaspoon contains: sodium 3 mg
- store between 20°-25°C (68°-77°F)
- tamper evident: do not use if foil seal over the mouth of the bottle is torn, broken, or missing.

Inactive ingredients

artificial flavor, citric acid, corn syrup FD&C blue #1, D&C red #33, glycerin, purified water sodium benzoate, sodium saccharin, sucralose, xanthan gum.

Questions?

877-434-2036

Distributed by: AccuDial® Pharmaceutical, Inc.
Palm Beach Gardens, FL 33408

PRINCIPAL DISPLAY PANEL - 118 mL Bottle Carton

ACCUDIAL®
Children's
Chest
Congestion

Guaifenesin
Oral Solution Expectorant

Relieves Chest Congestion
Thins & Loosens Mucus

Earth-Friendly
Package!

For Ages 4 yrs to under 12 yrs

Tamper Evident

Compares to
Mucinex® For Kids

GRAPE
FLAVOR

NDC 45014-163-04
4 FL. OZ. (118 mL)